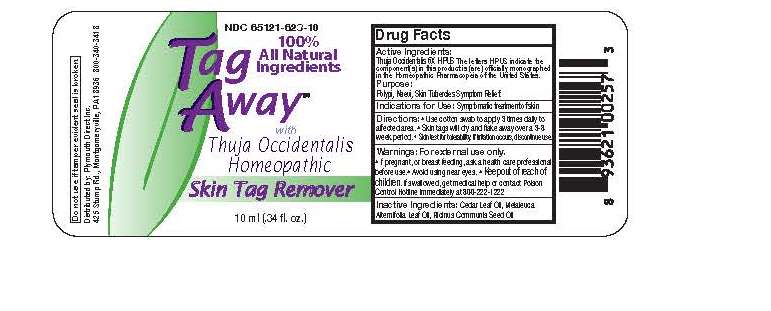 DRUG LABEL: Tag Away
NDC: 65121-623 | Form: LIQUID
Manufacturer: Pure Source
Category: homeopathic | Type: HUMAN OTC DRUG LABEL
Date: 20190102

ACTIVE INGREDIENTS: THUJA OCCIDENTALIS BARK 6 [hp_X]/10 mL
INACTIVE INGREDIENTS: CEDAR LEAF OIL; MELALEUCA ALTERNIFOLIA LEAF; RICINUS COMMUNIS SEED

Tag Away 10 ml

Warnings:

For external use only. If pregnant, or breast feeding, ask a health care professional before use. Avoid using near eyes. If swallowed, get medical help or contact poison control hotline immediately at 800-222-1222.

Directions:

Use cotton swab to apply 3 times daily to affected area. Skin tags will dry and flake away over a 3-8 week period. Skin test for tolerability. If irritation occurs, discontinue use.

Active Ingredients:

Thuja Occidentalis 6X HPUS

The letters HPUS indicate the components(s) in this product is (are) offically monographed in the Homeopathic Pharmacopeia of the United States

Inactive Ingredients:

Cedar leaf oil, Melaleuca Alternifolia Leaf Oil, Ricinus Communis Seed Oil

Purpose:

Polypi, Naevi, Skin Tubercles Symptom Relief.

Keep out of reach of children.

Directions:

Use cotton swab to apply 3 times daily to affected area. Skin tags will dry and flake away over a 3-8 week period. Skin test for tolerability. If irritation occurs, discontinue use.